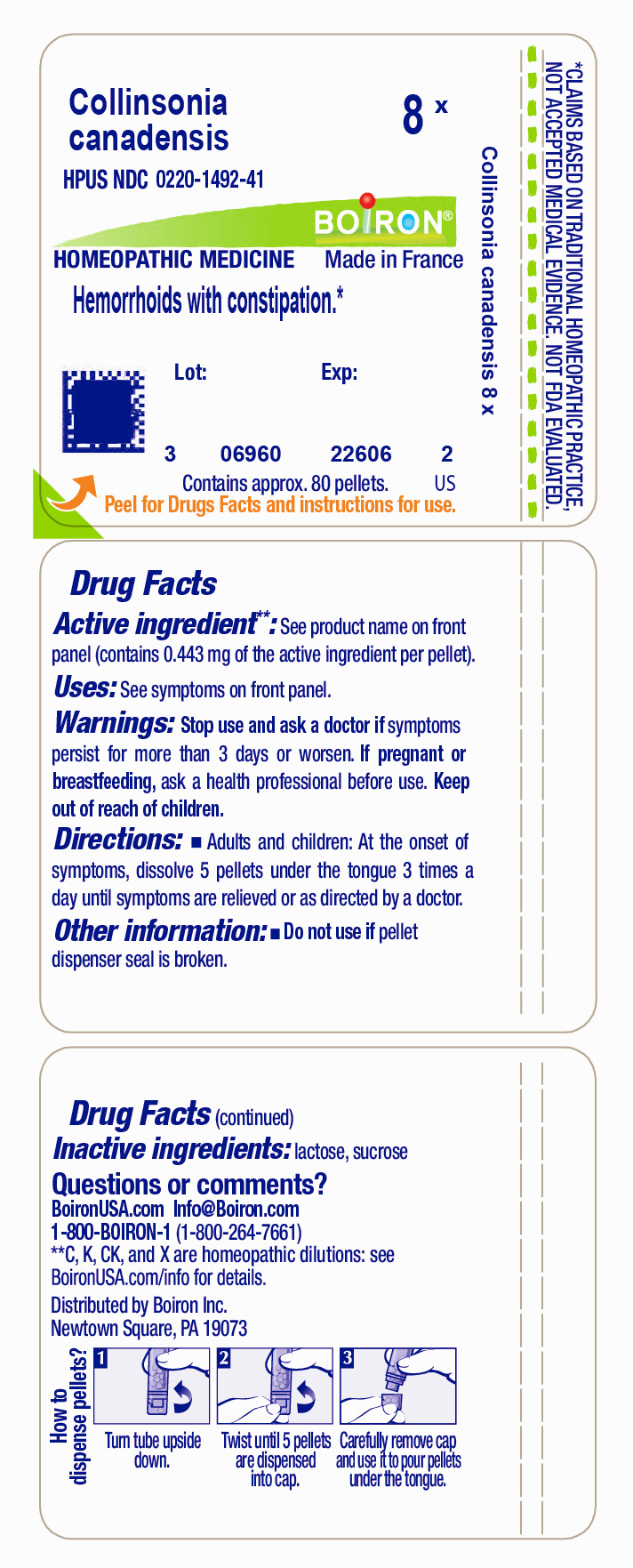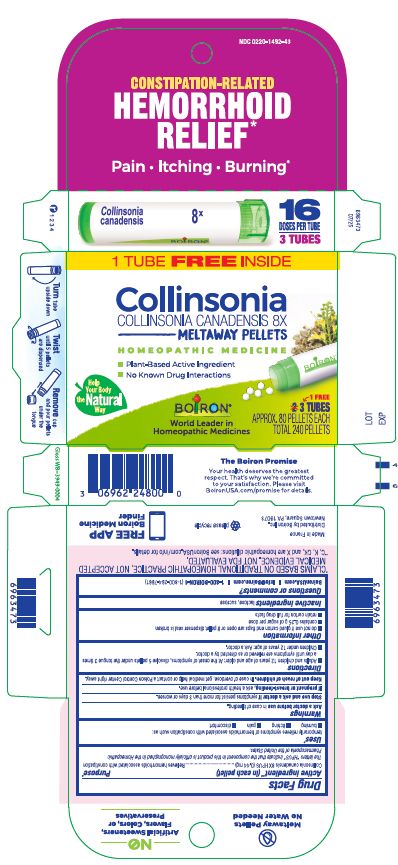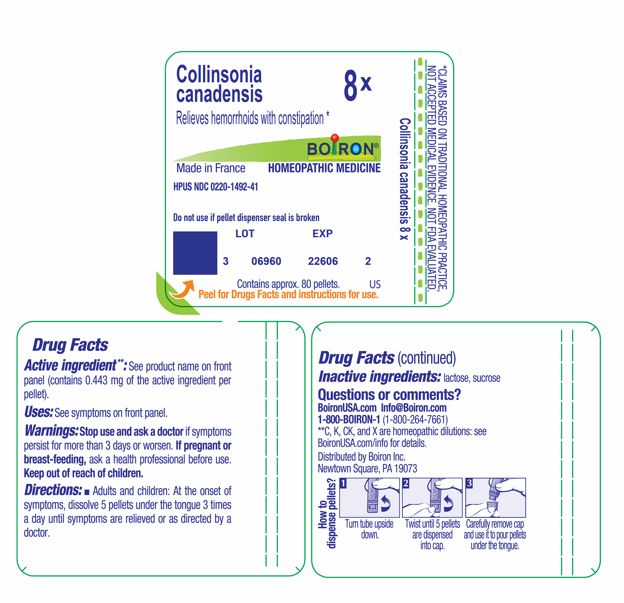 DRUG LABEL: Collinsonia canadensis
NDC: 0220-1492 | Form: PELLET
Manufacturer: Boiron
Category: homeopathic | Type: HUMAN OTC DRUG LABEL
Date: 20260210

ACTIVE INGREDIENTS: COLLINSONIA CANADENSIS ROOT 8 [hp_X]/8 [hp_X]
INACTIVE INGREDIENTS: SUCROSE; LACTOSE, UNSPECIFIED FORM

Collinsonia canadensis 8X

Active ingredient** (in each pellet)

Collinsonia canadensis 8X HPUS (0.44 mg)

The letters “HPUS” indicate that the component in this product is officially monographed in the Homeopathic Pharmacopoeia of the United States.

PURPOSE

Collinsonia canadensis 8X HPUS (0.44 mg)………Relieves hemorrhoids associated with constipation

Uses*

temporarily relieves symptoms of hemorrhoids associated with constipation such as:

- burning
- itching
- pain
- discomfort

Ask a doctor before use in case of bleeding.

Stop use and ask a doctor if symptoms persist for more than 3 days or worsen.

PREGNANCY OR BREAST FEEDING

If pregnant or breast-feeding, ask a health professional before use.

Keep out of reach of children. In case of overdose, get medical help or contact a Poison Control Center right away.

DOSAGE AND ADMINISTRATION

- Adults and children 12 years of age and older: At the onset of symptoms, dissolve 5 pellets under the tongue 3 times a day until symptoms are relieved or as directed by a doctor.
- Children under 12 years of age: Ask a doctor.

INACTIVE INGREDIENT

lactose, sucrose

QUESTIONS

BoironUSA.com

Info@Boiron.com

1-800-BOIRON-1 (1-800-264-7661)

Made in France

Distributed by Boiron Inc.

Newtown Square, PA 19073

do not use if glued carton end flaps are open or if pellet dispenser seal is broken

contains 0.25 g of sugar per dose

retain carton for full drug facts

Constipation-Related

HEMORRHOID RELIEF*

Pain Itching Burning*

1 Tube

3 Tubes

APPROX. 80 PELLET EACH

TOTAL 240 PELLETS

Turn tube upside down

Twist until 5 pellets are dispensed

Remove cap and pour pellets under the tongue

*CLAIMS BASED ON TRADITIONAL HOMEOPATHIC PRACTICE, NOT ACCEPTED MEDICAL EVIDENCE. NOT FDA EVALUATED.
**C, K, CK, and X are homeopathic dilutions: see BoironUSA.com/info for details.